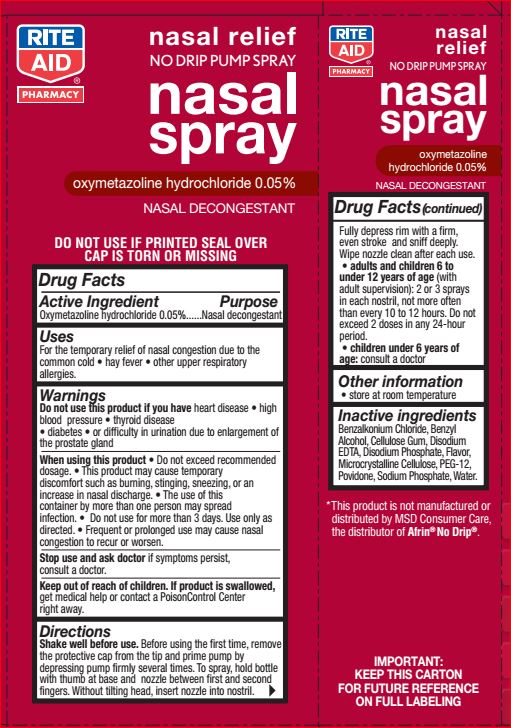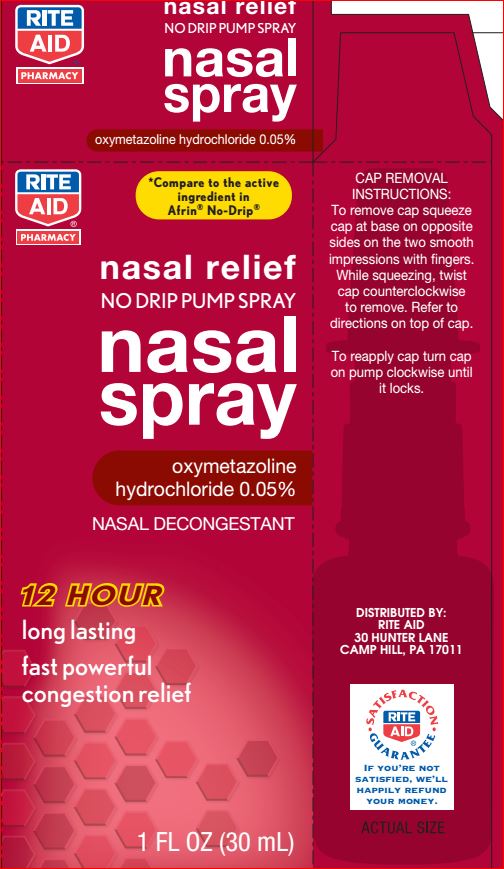 DRUG LABEL: Original No Drip Nasal
NDC: 11822-1231 | Form: LIQUID
Manufacturer: Rite Aid
Category: otc | Type: HUMAN OTC DRUG LABEL
Date: 20180615

ACTIVE INGREDIENTS: Oxymetazoline Hydrochloride 0.05 g/100 mL
INACTIVE INGREDIENTS: Benzalkonium Chloride; Benzyl Alcohol; EDETATE DISODIUM ANHYDROUS; SODIUM PHOSPHATE, DIBASIC, ANHYDROUS; CELLULOSE, MICROCRYSTALLINE; POLYETHYLENE GLYCOL 600; Povidone; Sodium Phosphate; water

Drug Facts

Active ingredient Purpose

Oxymetazoline Hydrochloride - 0.05% Nazal Decongestant

Uses

For the temporary relief of nasal congestion due to the
common cold • hay fever • other upper respiratory
allergies.

Warnings

Do not use this product if you have heart disease • high
blood pressure • thyroid disease
• diabetes • or difficulty in urination due to enlargement of
the prostate gland
When using this product • Do not exceed recommended
dosage. • This product may cause temporary
discomfort such as burning, stinging, sneezing, or an
increase in nasal discharge. • The use of this
container by more than one person may spread
infection. • Do not use for more than 3 days. Use only as
directed. • Frequent or prolonged use may cause nasal
congestion to recur or worsen.
Stop use and ask doctor if symptoms persist,
consult a doctor

Direction

Shake well before use. Before using the first time, remove
the protective cap from the tip and prime pump by
depressing pump firmly several times. To spray, hold bottle
with thumb at base and nozzle between first and second
fingers. Without tilting head, insert nozzle into nostril Fully depress rim with a firm,
even stroke and sniff deeply.
Wipe nozzle clean after each use.
• adults and children 6 to
under 12 years of age (with
adult supervision): 2 or 3 sprays
in each nostril, not more often
than every 10 to 12 hours. Do not
exceed 2 doses in any 24-hour
period.
• children under 6 years of
age: consult a doctor

Other information
• store at room temperature

Inactive ingredients

Benzalkonium Chloride
Benzyl Alcohol
Cellulose Gum
Disodium EDTA
Disodium Phosphate
Flavor
Microcrystalline Cellulose
PEG-12
Povidone
Sodium Phosphate
Water